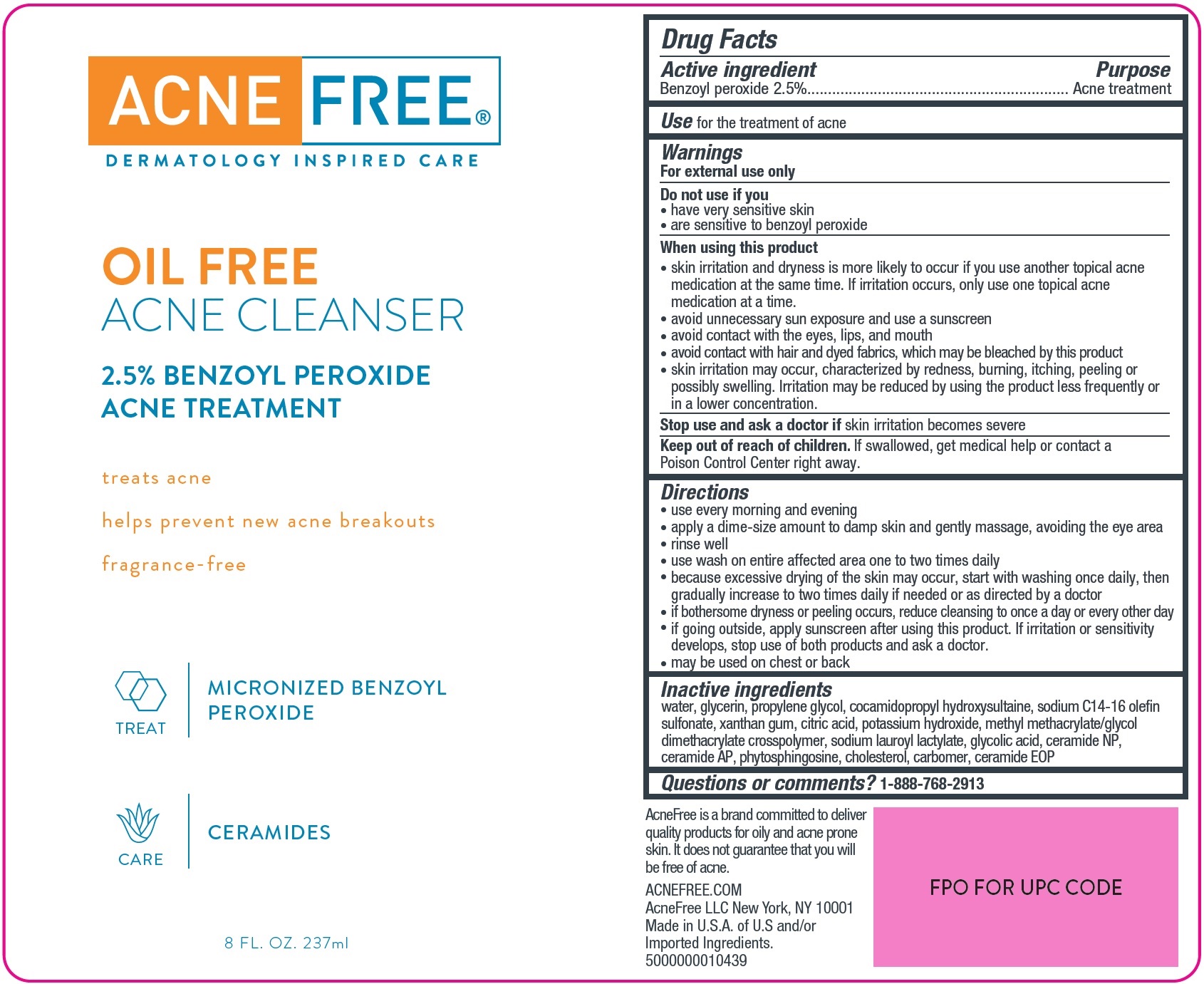 DRUG LABEL: Acne Free Oil Free Acne Cleanser 2.5 Benzoyl Peroxide
NDC: 80861-013 | Form: LIQUID
Manufacturer: AcneFree LLC
Category: otc | Type: HUMAN OTC DRUG LABEL
Date: 20250724

ACTIVE INGREDIENTS: BENZOYL PEROXIDE 25 mg/1 mL
INACTIVE INGREDIENTS: CERAMIDE AP; PHYTOSPHINGOSINE; CHOLESTEROL; CARBOMER HOMOPOLYMER, UNSPECIFIED TYPE; CERAMIDE 1; WATER; GLYCERIN; PROPYLENE GLYCOL; COCAMIDOPROPYL HYDROXYSULTAINE; SODIUM C14-16 OLEFIN SULFONATE; XANTHAN GUM; CITRIC ACID MONOHYDRATE; POTASSIUM HYDROXIDE; METHYL METHACRYLATE; SODIUM LAUROYL LACTYLATE; GLYCOLIC ACID; CERAMIDE NP

Acne Free Oil Free Acne Cleanser 2.5 % Benzoyl Peroxide

Active ingredient

Benzoyl peroxide 2.5%

Purpose

Acne treatment

Use

for the treatment of acne

Warnings

For external use only

Do not use

if you

• have very sensitive skin
• are sensitive to benzoyl peroxide

When using this product

- skin irritation and dryness is more likely to occur if you use another topical acne medication at the same time. If irritation occurs, only use one topical acne medication at a time.
- avoid unnecessary sun exposure and use a sunscreen
- avoid contact with the eyes, lips, and mouth
- avoid contact with hair and dyed fabrics, which may be bleached by this product
- skin irritation may occur, characterized by redness, burning, itching, peeling or possibly swelling. Irritation may be reduced by using the product less frequently or in a lower concentration.

Stop use and ask a doctor if

skin irritation becomes severe

Keep out of reach of children.

If swallowed, get medical help or contact a Poison Control Center right away.

Directions

- use every morning and evening
- apply a dime-size amount to damp skin and gently massage, avoiding the eye area
- rinse well
- use wash on entire affected area one to two times daily
- because excessive drying of the skin may occur, start with washing once daily, then gradually increase to two times daily if needed or as directed by a doctor
- if bothersome dryness or peeling occurs, reduce cleansing to once a day or every other day
- if going outside, apply sunscreen after using this product. If irritation or sensitivity develops, stop use of both products and ask a doctor.
- may be used on chest or back

Questions or comments?

water, glycerin, propylene glycol, cocamidopropyl hydroxysultaine, sodium C14-16 olefin sulfonate, xanthan gum, citric acid, potassium hydroxide, methyl methacrylate/glycol dimethacrylate crosspolymer, sodium lauroyl lactylate, glycolic acid, ceramide NP, ceramide AP, phytosphingosine, cholesterol, carbomer, ceramide EOP

Questions or comments?

1-888-768-2913